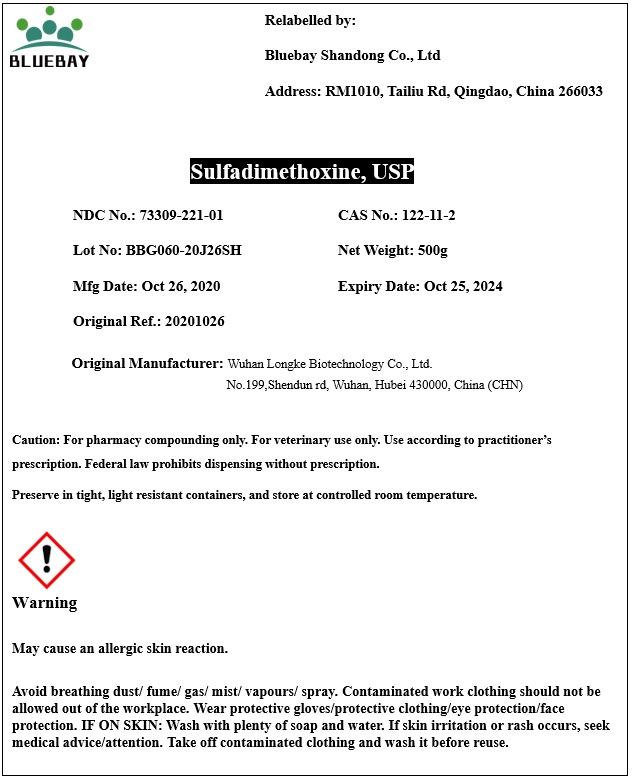 DRUG LABEL: Sulfadimethoxine
NDC: 73309-221 | Form: POWDER
Manufacturer: BLUEBAY SHANDONG CO.,LTD
Category: other | Type: BULK INGREDIENT
Date: 20210128

ACTIVE INGREDIENTS: SULFADIMETHOXINE 1 g/1 g

Sulfadimethoxine